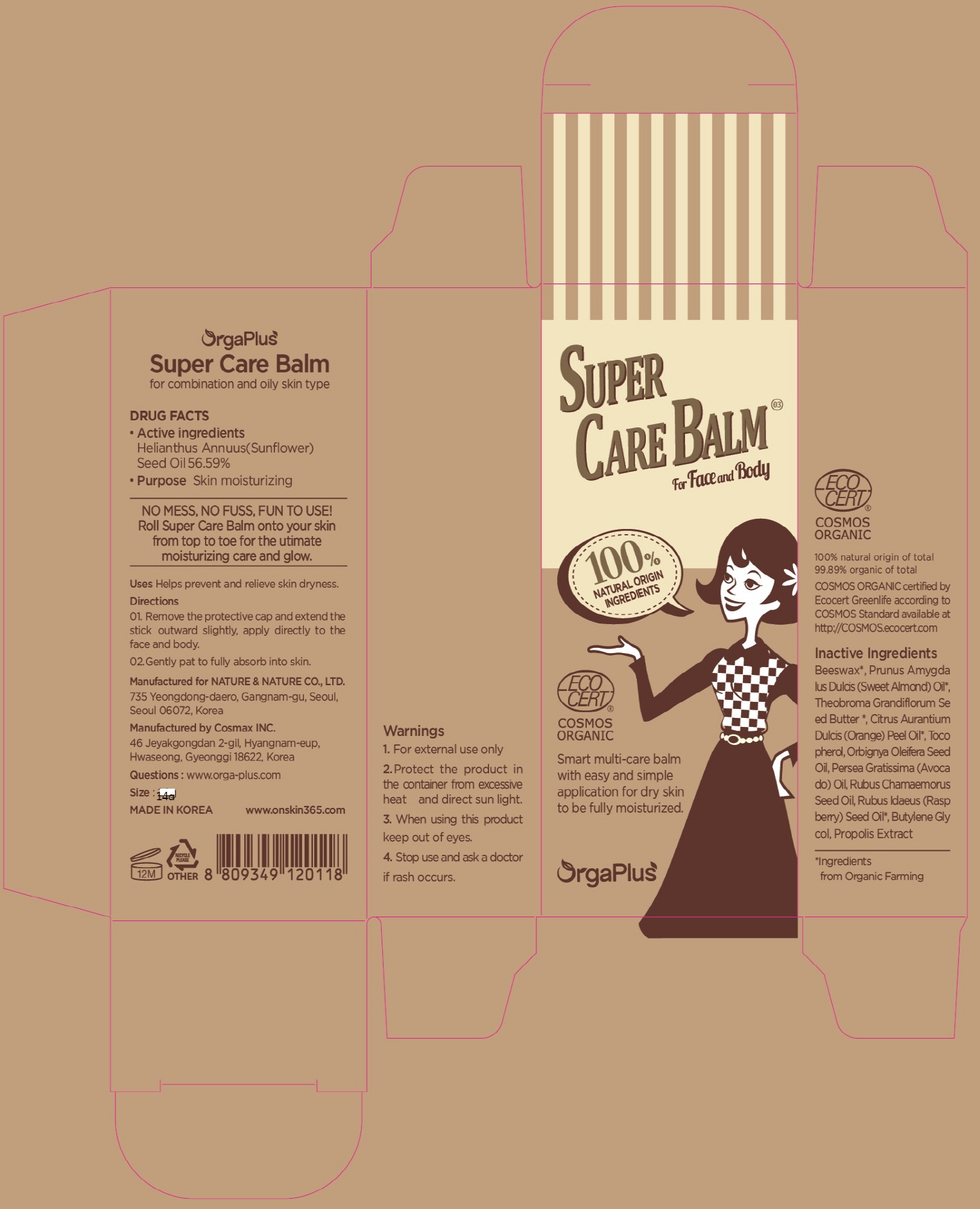 DRUG LABEL: OrgaPlus Super Care Balm for combination and oi ly skin type

NDC: 69777-180 | Form: STICK
Manufacturer: BLUEZONWIDE CO.,LTD
Category: otc | Type: HUMAN OTC DRUG LABEL
Date: 20250205

ACTIVE INGREDIENTS: SUNFLOWER OIL 7.92 g/14 g
INACTIVE INGREDIENTS: APIS MELLIFERA; ORANGE OIL

ACTIVE INGREDIENT

Active ingredients: Helianthus Annuus (Sunflower) Seed Oil 56.59%

INACTIVE INGREDIENT

Inactive ingredients:

Beeswax, Prunus Amygdalus Dulcis (Sweet Almond) Oil, Theobroma Grandiflorum Seed Butter, Citrus Aurantium Dulcis (Orange) Peel Oil, Tocopherol, Orbignya Oleifera Seed Oil, Persea Gratissima (Avocado) Oil, Rubus Chamaemorus Seed Oil, Rubus Idaeus (Raspberry) Seed Oil, Butylene Glycol, Propolis Extract

PURPOSE

Purpose: Skin moisturizing

WARNINGS

-For external use only

-Protect the product in the container from excessive heat and direct sun light.

-When using this product keep out of eyes.

-Stop use and ask a doctor if rash occurs.

KEEP OUT OF REACH OF CHILDREN

Uses

Helps prevent and relieve skin dryness.

Directions

01. Remove the protective cap and extend the stick outward slightly, apply directly to the face and body.

02. Gently pat to fully absorb into skin.

QUESTIONS

www.orga-plus.com